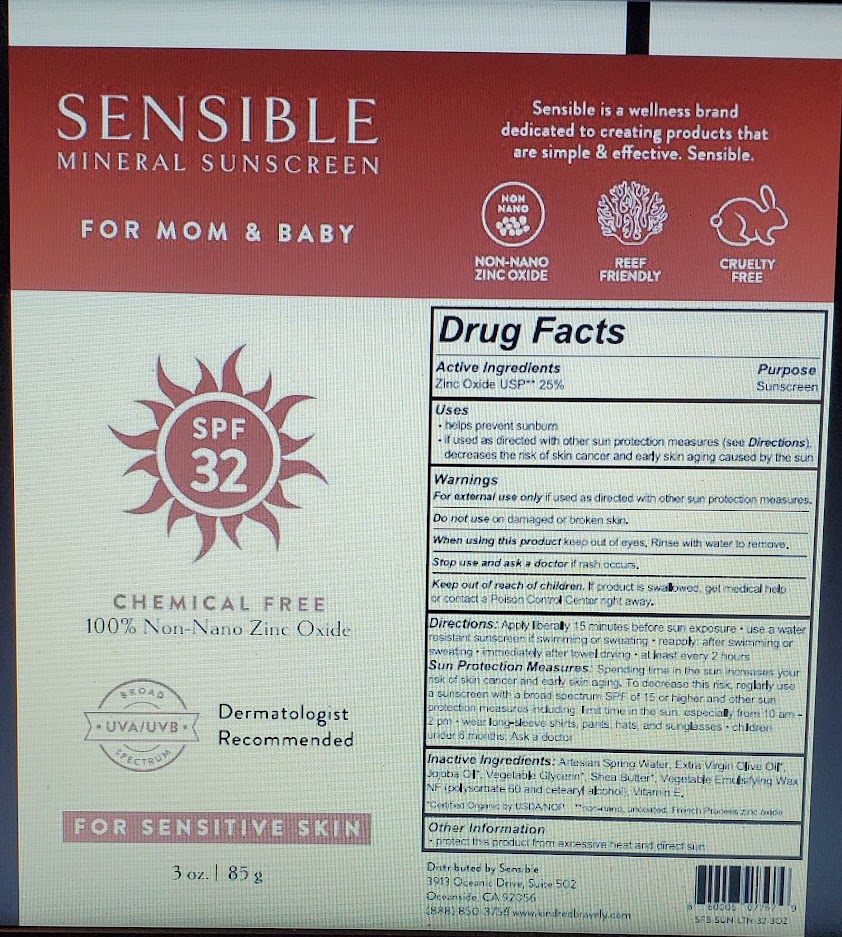 DRUG LABEL: Sensible SPF 32 Mineral Sunscreen
NDC: 73369-1501 | Form: CREAM
Manufacturer: Kabana Skin Care
Category: otc | Type: HUMAN OTC DRUG LABEL
Date: 20241023

ACTIVE INGREDIENTS: ZINC OXIDE 25 g/100 g
INACTIVE INGREDIENTS: SHEA BUTTER 1.93 g/100 g; ALPHA-TOCOPHEROL 1.38 g/100 g; OLIVE OIL 26.95 g/100 g; POLYSORBATE 60 1.125 g/100 g; CETOSTEARYL ALCOHOL 1.125 g/100 g; GLYCERIN 3.75 g/100 g; JOJOBA OIL 3.75 g/100 g; WATER 35 g/100 g

Drug Facts

Active Ingredients

Zinc Oxide USP** 25%

Purpose

Sunscreen

Uses

• helps prevent sunburn
• if used as directed with other sun protection measures (see Directions), decreases the risk of skin cancer and early skin aging caused by the sun

Do not use on damaged or broken skin

When using this product keep out of eyes. Rinse with water to remove.

Stop use and ask a doctor if rash occurs

Keep out of reach of children, if product is swallowed, get medical help or contact a Poison Control Center right away.

Warnings

For external use only if used as directed with other sun protection measures

Directions

• apply liberally 15 minutes before sun exposure
• use a water resistant sunscreen if swimming or sweating
• reapply:

• after swimming or sweating
• immediately after towel drying
• at least every 2 hours

• Sun Protection Measures. Spending time in the sun increases your risk of skin cancer and early skin aging. To decrease this risk, regularly use a sunscreen with a Broad Spectrum SPF value of 15 or higher and other sun protection measures including:

• limit time in the sun, especially from 10 AM – 2 PM.
• wear long-sleeved shirts, pants, hats and sunglasses.

• Children under 6 months. Ask a doctor.

DOSAGE AND ADMINISTRATION

- apply liberally 15 minutes before sun exposure
- use a water resistant sunscreen if swimming or sweating
- reapply:
- after swimming or sweating
- immediately after towel drying
- at least every 2 hours.
- Sun Protection Measures. Spending time in the sun increases your risk of skin cancer and early skin aging. To decrease this risk, regularly use a sunscreen with a Broad Spectrum SPF value of 15 or higher and other sun protection measures including:
- Limit time in the sun, especially from 10 AM – 2 PM.
- Wear long-sleeved shirts, pants, hats and sunglasses.
- Children under 6 months. Ask a doctor

Inactive Ingredients

Artesian Spring Water, Extra Virgin Olive Oil*, Vegetable Gycerin*, Jojoba Oil*, Shea Butter*, Vegetable Emulsifying Wax NF# (polysorbate 60 and cetearyl alcohol), Vitamin E.

*Certified Organic by USDA/NOP **non-nano, uncoated, French Process zinc oxide

Other Information

• protect this product from excessive heat and direct sun